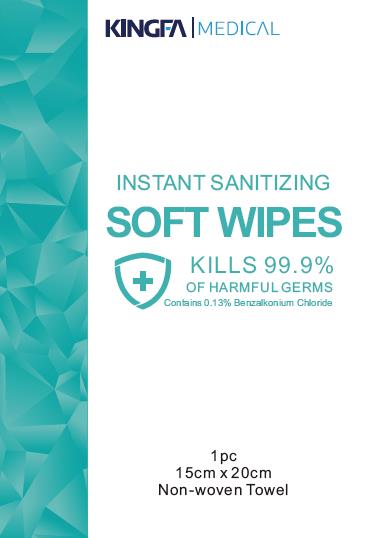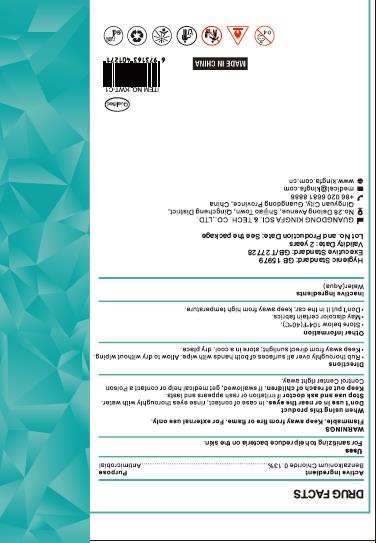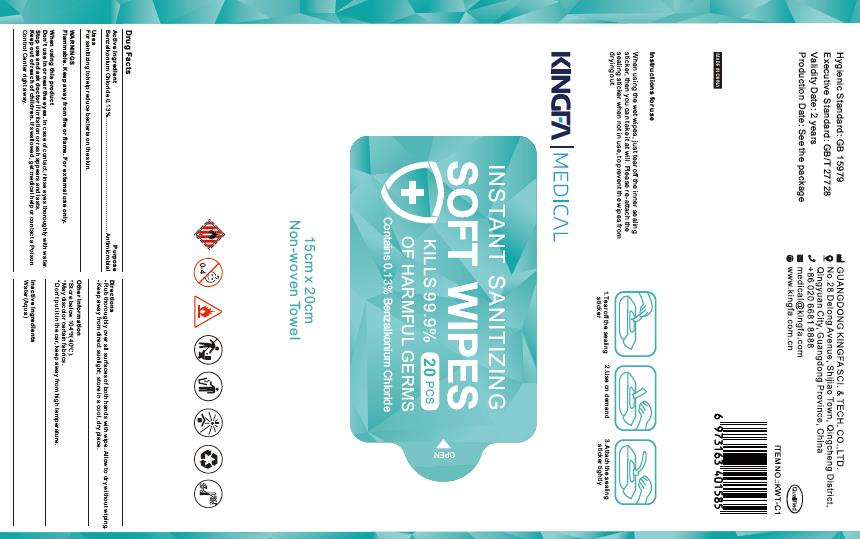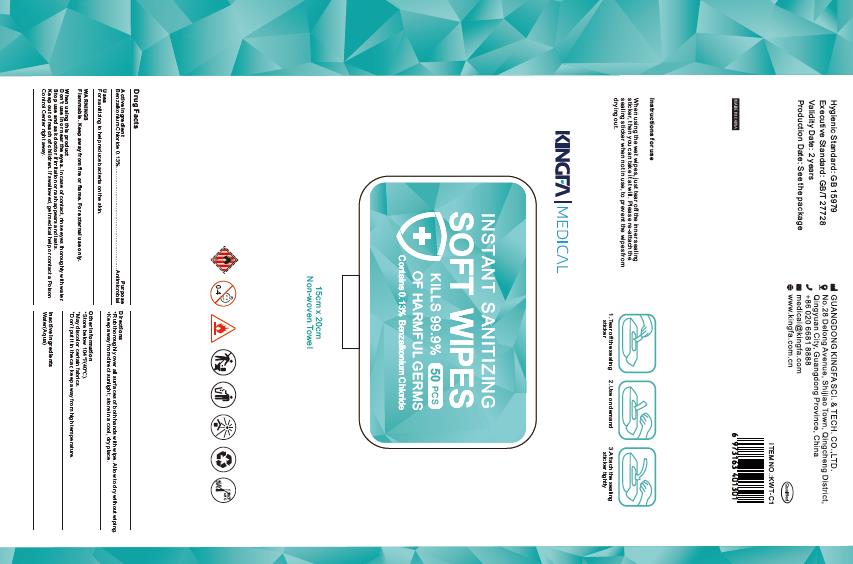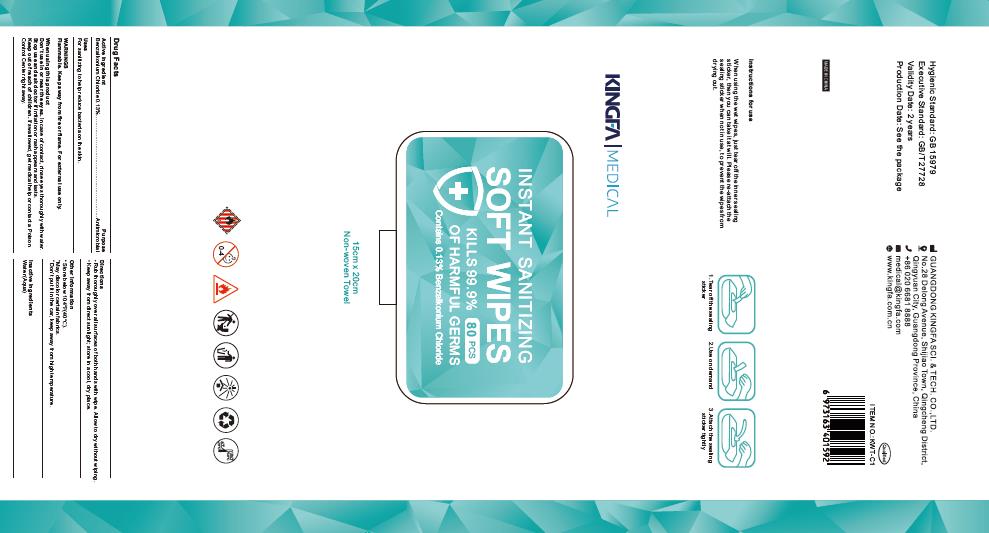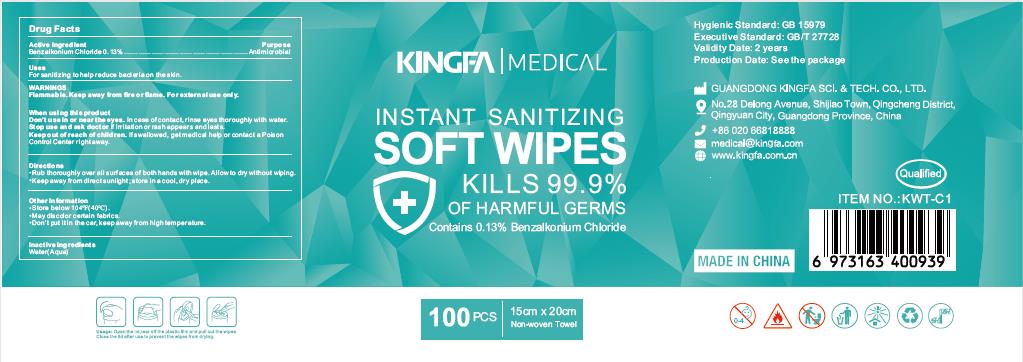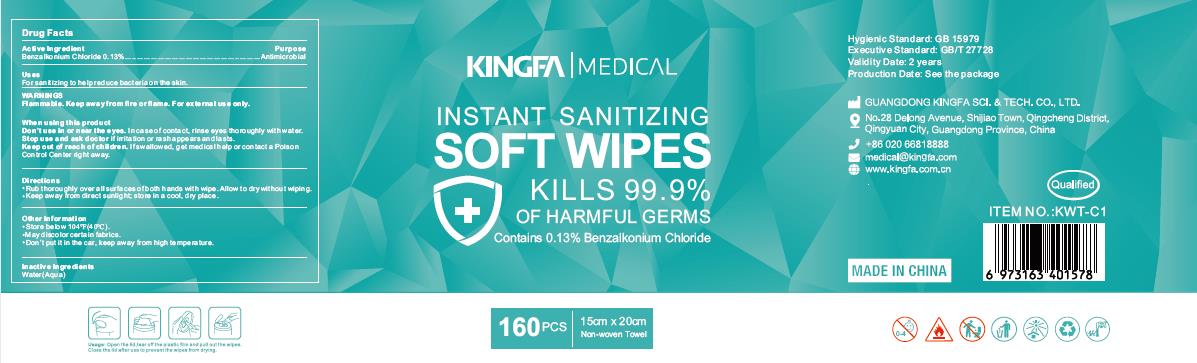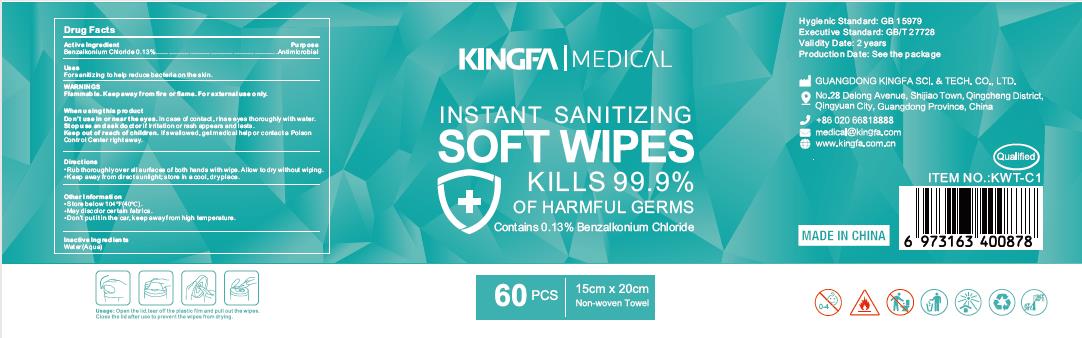 DRUG LABEL: Instant Sanitizing Soft Wipes
NDC: 80974-003 | Form: SWAB
Manufacturer: GUANGDONG KINGFA SCI.&TECH.CO.,LTD.
Category: otc | Type: HUMAN OTC DRUG LABEL
Date: 20201224

ACTIVE INGREDIENTS: BENZALKONIUM CHLORIDE 0.13 g/100 g
INACTIVE INGREDIENTS: WATER

Benzalkonium chloride jinfa

Active Ingredient(s)

Benzalkonium chloride 0.13%

Purpose

Purpose: Antimicrobial

Uses

For sanitizing to help reduce bacteria on the skin.

Warnings

Flammable.Keep away from fire or flame. For external use only.

When using this product, avoid contact with eyes.

Do not use

in or near the eyes. In case of contact, rinse eyes thoroughly with water.

Stop use and ask a doctor if irritation or rash appears and lasts.

Keep out of reach of children. If swallowed, get medical help or contact a Poison Control Center right away.

Directions

- Rub thoroughly over all surfaces of both hands with wipe. Allow to dry without wiping.
- Keep away from dirct sunlight; store in a cool, dry place.

Other information

- Store below 104F(40C)
- May discolor certain fabrics.
- Don't put it in the car, keep away from high temperature.

Inactive ingredients

Water(Aqua)

Package Label - Principal Display Panel

1 PCS NDC 80974-003-01

20PCS NDC 80974-003-02

50PCS NDC 80974-003-03

80PCS NDC 80974-003-04

60PCS NDC 80974-003-05

100PCS NDC 80974-003-06

160PCS NDC 80974-003-07